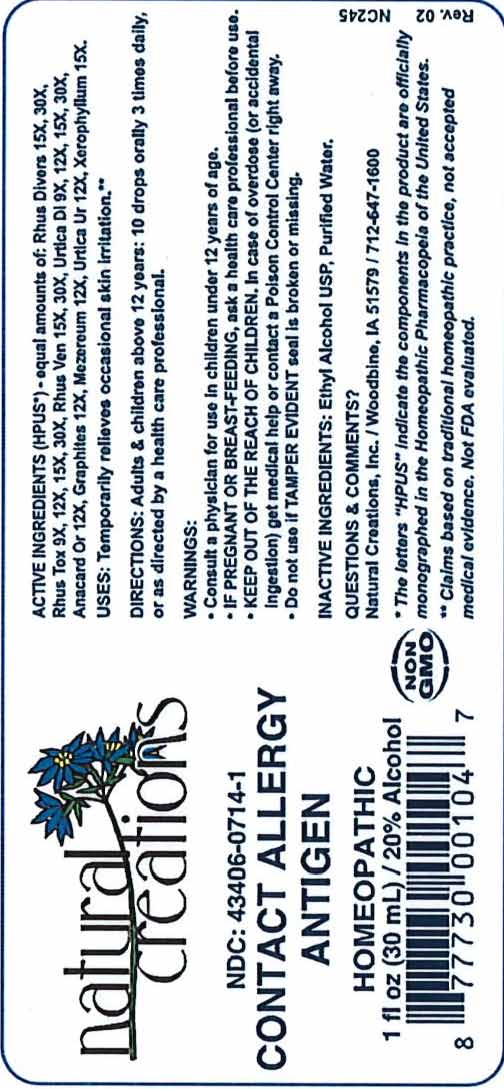 DRUG LABEL: CONTACT ALLERGY ANTIGEN
NDC: 43406-0714 | Form: LIQUID
Manufacturer: Natural Creations, Inc.
Category: homeopathic | Type: HUMAN OTC DRUG LABEL
Date: 20251201

ACTIVE INGREDIENTS: TOXICODENDRON DIVERSILOBUM LEAF 30 [hp_X]/1 mL; TOXICODENDRON PUBESCENS LEAF 30 [hp_X]/1 mL; TOXICODENDRON VERNIX LEAFY TWIG 30 [hp_X]/1 mL; URTICA DIOICA 30 [hp_X]/1 mL; SEMECARPUS ANACARDIUM FRUIT 12 [hp_X]/1 mL; GRAPHITE 12 [hp_X]/1 mL; DAPHNE MEZEREUM BARK 12 [hp_X]/1 mL; URTICA URENS 12 [hp_X]/1 mL; XEROPHYLLUM ASPHODELOIDES 15 [hp_X]/1 mL
INACTIVE INGREDIENTS: ALCOHOL; WATER

CONTACT ALLERGY ANTIGEN

ACTIVE INGREDIENT

ACTIVE INGREDIENTS (*HPUS)- equal amounts of: Rhus Divers 15X, 30X, Rhus Tox 9X, 12X, 15X, 30X, Rhus Ven 15X, 30X, Urtica Di 9x, 12X, 15X, 30X, Anacard Or 12X, Graphites 12X, Mezereum 12X, Urtica Ur 12X, Xerophyllum 15X.

PURPOSE

USES: Temporarily relieves occasional skin irritation.**

INDICATIONS AND USAGE

USES: Temporarily relieves occasional skin irritation.**

DOSAGE AND ADMINISTRATION

DIRECTIONS: Adults & children above 12 years: 10 drops orally 3 times daily, or as directed by a health care professional.

KEEP OUT OF REACH OF CHILDREN

KEEP OUT OF THE REACH OF CHILDREN. In case of overdose (or accidental ingestion) get medical help or contact a Poison Control Center right away.

WARNINGS:

- Consult a physician for use in children under 12 years of age.
- IF PREGNANT OR BREAST-FEEDING, ask a health care professional before use.
- KEEP OUT OF THE REACH OF CHILDREN. In case of overdose (or accidental ingestion) get medical help or contact a Poison Control Center right away.
- Do not use if TAMPER EVIDENT seal is broken or missing.

INACTIVE INGREDIENTS: Ethyl Alcohol USP, Purified Water.

QUESTIONS & COMMENTS?

Natural Creations, Inc. / Woodbine, IA 51579 / 712-647-1600

REFERENCES

* The letters "HPUS" indicate the components in the product are officially monographed in the Homeopathic Pharmacopeia of the United States.

**Claims based on traditional homeopathic practice, not accepted medical evidence. Not FDA evaluated.

PACKAGE LABEL

NDC: 43406-0714-1

CONTACT ALLERGY ANTIGEN

HOMEOPATHIC

1 fl oz (3o mL) / 20% alcohol

UPC: 87773001047 NON GMO Logo